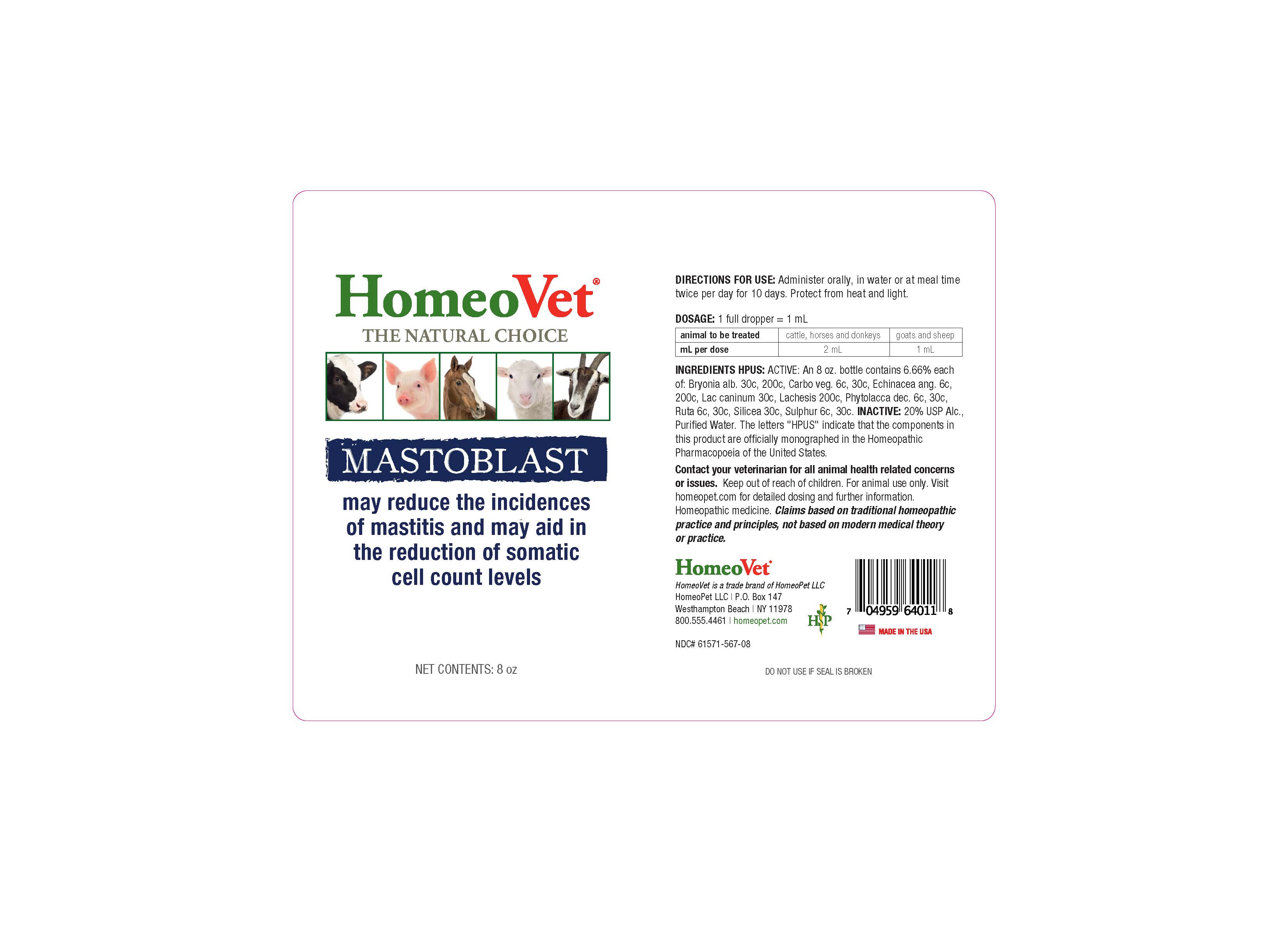 DRUG LABEL: Mastoblast
NDC: 61571-567 | Form: LIQUID
Manufacturer: HomeoPet LLC
Category: homeopathic | Type: OTC ANIMAL DRUG LABEL
Date: 20251211

ACTIVE INGREDIENTS: BRYONIA ALBA ROOT 30 [hp_C]/120 mL; ACTIVATED CHARCOAL 6 [hp_C]/120 mL; ECHINACEA ANGUSTIFOLIA 6 [hp_C]/120 mL; CANIS LUPUS FAMILIARIS MILK 30 [hp_C]/120 mL; LACHESIS MUTA VENOM 200 [hp_C]/120 mL; PHYTOLACCA AMERICANA ROOT 6 [hp_C]/120 mL; SILICON DIOXIDE 30 [hp_C]/120 mL; SULFUR 6 [hp_C]/120 mL; RUTA GRAVEOLENS FLOWERING TOP 6 [hp_C]/120 mL
INACTIVE INGREDIENTS: ALCOHOL; WATER

Mastoblast

INDICATIONS AND USAGE

May reduce the incidences of mastitis and may aid in the reduction of somatic cell count levels

DIRECTIONS FOR USE

Administer orally, in water or at meal time twice per day for 10 days. Protect from heat and light.

DOSAGE: 1 full dropper = 1 mL

animal to be treated | cattle, horses and donkeys | goats and sheep
mL per dose | 2 mL | 1 mL

INGREDIENTS

Bryonia alb 30c, 200c, Carbo veg. 6c, 30c, Echinacea ang 6c, 200c, Lac caninum 30c, Lachesis 200c, Phytolacca dec. 6c, 200c, Silica 30c, Sulphur 6c, 30c, Ruta 6c, 30c

INACTIVE INGREDIENT

Alcohol, Water

ASK DOCTOR

Contactyour veterinarian for all animal health related concerns or issues.

Keep out of reach of children. For animal use only. Visit homeopet.com for detailed dosing and further information. Homeopathic medicine.